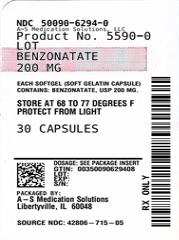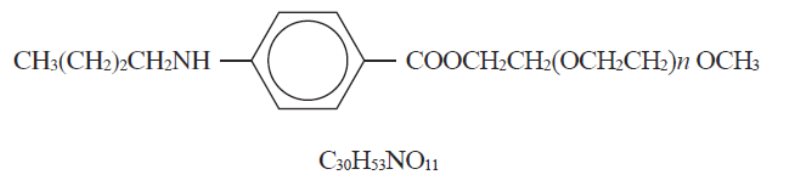 DRUG LABEL: Benzonatate
NDC: 50090-6294 | Form: CAPSULE
Manufacturer: A-S Medication Solutions
Category: prescription | Type: HUMAN PRESCRIPTION DRUG LABEL
Date: 20260213

ACTIVE INGREDIENTS: BENZONATATE 200 mg/1 1
INACTIVE INGREDIENTS: D&C YELLOW NO. 10; GELATIN; GLYCERIN; LECITHIN, SOYBEAN; LIGHT MINERAL OIL; PROPYLENE GLYCOL; SHELLAC; TITANIUM DIOXIDE; AQUA

Benzonatate Capsules, USP

DESCRIPTION

Benzonatate capsules, USP, a non-narcotic oral antitussive agent, is 2, 5, 8, 11, 14, 17, 20, 23, 26- onaoxaoctacosan-28-ylp-(butylamino) benzoate; with a molecular weight of 603.7. Each benzonatate capsules, USP for oral administration contains 100 mg or 200 mg benzonatate, USP. In addition, each capsule contains the following inactive ingredients: D&C Yellow #10, gelatin, glycerin, lecithin, light mineral oil, propylene glycol, purified water, shellac glaze, titanium dioxide, and white edible ink.

CLINICAL PHARMACOLOGY

Benzonatate capsules act peripherally by anesthetizing the stretch receptors located in the respiratory passages, lungs, and pleura by dampening their activity and thereby reducing the cough reflex at its source. It begins to act within 15 to 20 minutes and its effect lasts for 3 to 8 hours. Benzonatate capsules have no inhibitory effect on the respiratory center in recommended dosage.

INDICATIONS AND USAGE

Benzonatate capsules, USP are indicated for the symptomatic relief of cough.

CONTRAINDICATIONS

Hypersensitivity to benzonatate or related compounds.

WARNINGS

Hypersensitivity

Severe hypersensitivity reactions (including bronchospasm, laryngospasm and cardiovascular collapse) have been reported which are possibly related to local anesthesia from sucking or chewing the capsule instead of swallowing it. Severe reactions have required intervention with vasopressor agents and supportive measures.

Psychiatric Effects

Isolated instances of bizarre behavior, including mental confusion and visual hallucinations, have also been reported in patients taking Benzonatate capsules in combination with other prescribed drugs.

Accidental Ingestion and Death in Children

Keep benzonatate capsules out of reach of children. Accidental ingestion of benzonatate capsules resulting in death has been reported in children below age 10. Signs and symptoms of overdose have been reported within 15-20 minutes and death has been reported within one hour of ingestion. If accidental ingestion occurs, seek medical attention immediately (see OVERDOSAGE).

PRECAUTIONS

Benzonatate is chemically related to anesthetic agents of the para-amino-benzoic acid class (e.g. procaine; tetracaine) and has been associated with adverse CNS effects possibly related to a prior sensitivity to related agents or interaction with concomitant medication.

Information for Patients:

Swallow benzonatate capsules whole. Do not break, chew, dissolve, cut, or crush benzonatate capsules. Release of benzonatate from the capsule in the mouth can produce a temporary local anesthesia of the oral mucosa and choking could occur. If numbness or tingling of the tongue, mouth, throat, or face occurs, refrain from oral ingestion of food or liquids until the numbness has resolved. If the symptoms worsen or persist, seek medical attention.

Keep benzonatate capsules out of reach of children. Accidental ingestion resulting in death has been reported in children. Signs and symptoms of overdose have been reported within 15-20 minutes and death has been reported within one hour of ingestion. Signs and symptoms may include restlessness, tremors, convulsions, coma and cardiac arrest. If accidental ingestion occurs, seek medical attention immediately.

Overdosage resulting in death may occur in adults.

Do not exceed a single dose of 200 mg and a total daily dosage of 600 mg. If you miss a dose of benzonatate capsules, skip that dose and take the next dose at the next scheduled time. Do not take 2 doses of benzonatate capsules at one time.

Usage in Pregnancy

PREGNANCY CATEGORY C

Animal reproduction studies have not been conducted with benzonatate capsules. It is also not known whether benzonatate capsules can cause fetal harm when administered to a pregnant woman or can affect reproduction capacity. Benzonatate capsules should be given to a pregnant woman only if clearly needed.

Nursing Mothers

It is not known whether this drug is excreted in human milk. Because many drugs are excreted in human milk caution should be exercised when benzonatate capsules are administered to a nursing woman.

Carcinogenesis, Mutagenesis, Impairment of Fertility

Carcinogenicity, mutagenicity, and reproduction studies have not been conducted with benzonatate capsules..

Pediatric Use

Safety and effectiveness in children below the age of 10 have not been established. Accidental ingestion resulting in death has been reported in children below age 10. Keep out of reach of children.

ADVERSE REACTIONS

Potential Adverse Reactions to benzonatate capsules may include:

Hypersensitivity reactionsincluding bronchospasm, laryngospasm, cardiovascular collapse possibly related to local anesthesia from chewing or sucking the capsule.

CNS

sedation; headache; dizziness; mental confusion; visual hallucinations.

GI

constipation; nausea; GI upset.

Dermatologic

pruritus; skin eruptions.

Other

nasal congestion; sensation of burning in the eyes; vague “chilly” sensation; numbness of the chest; hypersensitivity.

Deliberate or accidental overdose has resulted in death, particularly in children.

Hypersensitivity reactions

including bronchospasm, laryngospasm, cardiovascular collapse possibly related to local anesthesia from chewing or sucking the capsule.

OVERDOSAGE

Intentional and unintentional overdose may result in death, particularly in children.

The drug is chemically related to tetracaine and other topical anesthetics and shares various aspects of their pharmacology and toxicology. Drugs of this type are generally well absorbed after ingestion.

Signs and Symptoms

The signs and symptoms of overdose of benzonatate capsules have been reported within 15-20 minutes. If capsules are chewed or dissolved in the mouth, oropharyngeal anesthesia will develop rapidly, which may cause choking and airway compromise.

CNS stimulation may cause restlessness and tremors which may proceed to clonic convulsions followed by profound CNS depression. Convulsions, coma, cerebral edema and cardiac arrest leading to death have been reported within 1 hour of ingestion.

Treatment

In case of overdose, seek medical attention immediately. Evacuate gastric contents and administer copious amounts of activated charcoal slurry. Even in the conscious patient, cough and gag reflexes may be so depressed as to necessitate special attention to protection against aspiration of gastric contents and orally administered materials. Convulsions should be treated with a short-acting barbiturate given intravenously and carefully titrated for the smallest effective dosage. Intensive support of respiration and cardiovascular-renal function is an essential feature of the treatment of severe intoxication from overdosage.

Do not use CNS stimulants.

DOSAGE AND ADMINISTRATION

Adults and Children over 10 years of age: Usual dose is one 100 mg or 200 mg capsule three times a day as needed for cough. If necessary to control cough, up to 600 mg daily in three divided doses may be given. Benzonatate capsules should be swallowed whole.Benzonatate capsules are not to be broken, chewed, dissolved, cut or crushed.

HOW SUPPLIED

Product: 50090-6294

NDC: 50090-6294-0 30 CAPSULE in a BOTTLE

NDC: 50090-6294-1 45 CAPSULE in a BOTTLE

NDC: 50090-6294-2 15 CAPSULE in a BOTTLE